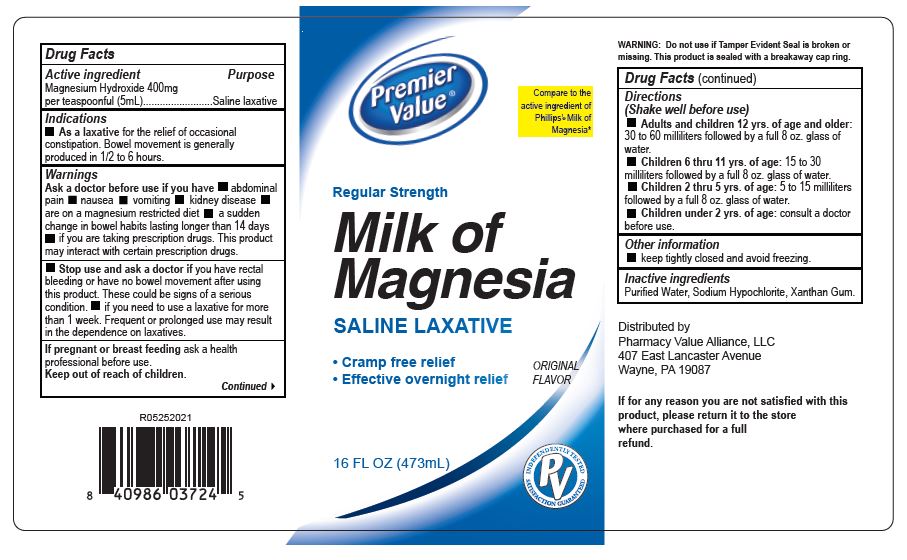 DRUG LABEL: Premier Value Milk of Magnesia
NDC: 68016-850 | Form: SUSPENSION
Manufacturer: Pharmacy Value Alliance, LLC
Category: otc | Type: HUMAN OTC DRUG LABEL
Date: 20231220

ACTIVE INGREDIENTS: MAGNESIUM HYDROXIDE 80 mg/1 mL
INACTIVE INGREDIENTS: WATER

Premier Value Milk of Magnesia USP

Drug Facts

Active ingredient

Magnesium Hydroxide 400 mg per teaspoon (5 mL)

Purpose

Antacid/Saline Laxative

Use

As an antacid: helps relieve acid ingestion, heartburn and sour stomach.

As a laxative: For the temporary relief of occasional constipation. Bowel movement is generally produced in 1.2 to 6 hours.

WARNINGS Ask a doctor before use if you have.

Abdominal pain, nausea, vomiting, kidney desease, are on a magnesium restricted diet, a sudden change in bowel habits lasting longer than 14 days, if you are taking prescription drugs. Antacids may interact with certain prescription drugs.

Stop use and ask a doctor.

If you have rectal bleeding or have no bowel movement after using this product. this could be signs of a serious codition, if you need to use a laxative for more than one week. Frequent or prolonged use may result in the dependence on laxatives.

When using this product.

As an antacid, do not take more than the maximum recomended daily dose in a 24 hr. period or take the maximum dose for more than two weeks, except under the advise of a doctor. May have laxative effect.

If pregnant or breastfeeding ask a health professional before use.

Keep out of reach of children.

In the case of accidental overdose, seek professional assistance or contact a Poison Control Center immediately.

Directions (Shake well before use)

As an antacid: Adults and children 12 yrs. of age and older: 1 to 3 teaspoonfuls with a little water, or as directed by a doctor.

As a laxative: Adults and children 12 yrs. of age and older: 1 to 4 tablespoonfuls followed by a full 8 oz. glass of water.

Children 6 thru 11 yr. of age: 1 to 2 tablespoonfuls followed by a full 8 oz. glass of water.

children 2 thru 5 yrs. of age: 1 to 3 teaspoonfuls followed by a full 8 oz. glass of water.

Children under 2 yrs. of age: consult a doctor before use.

Other information

acid neutralizing capacilty: 10.0 mEq per teaspoon.

keep tightly closed and avoid freezing.

Inactive ingredient.

Purified water